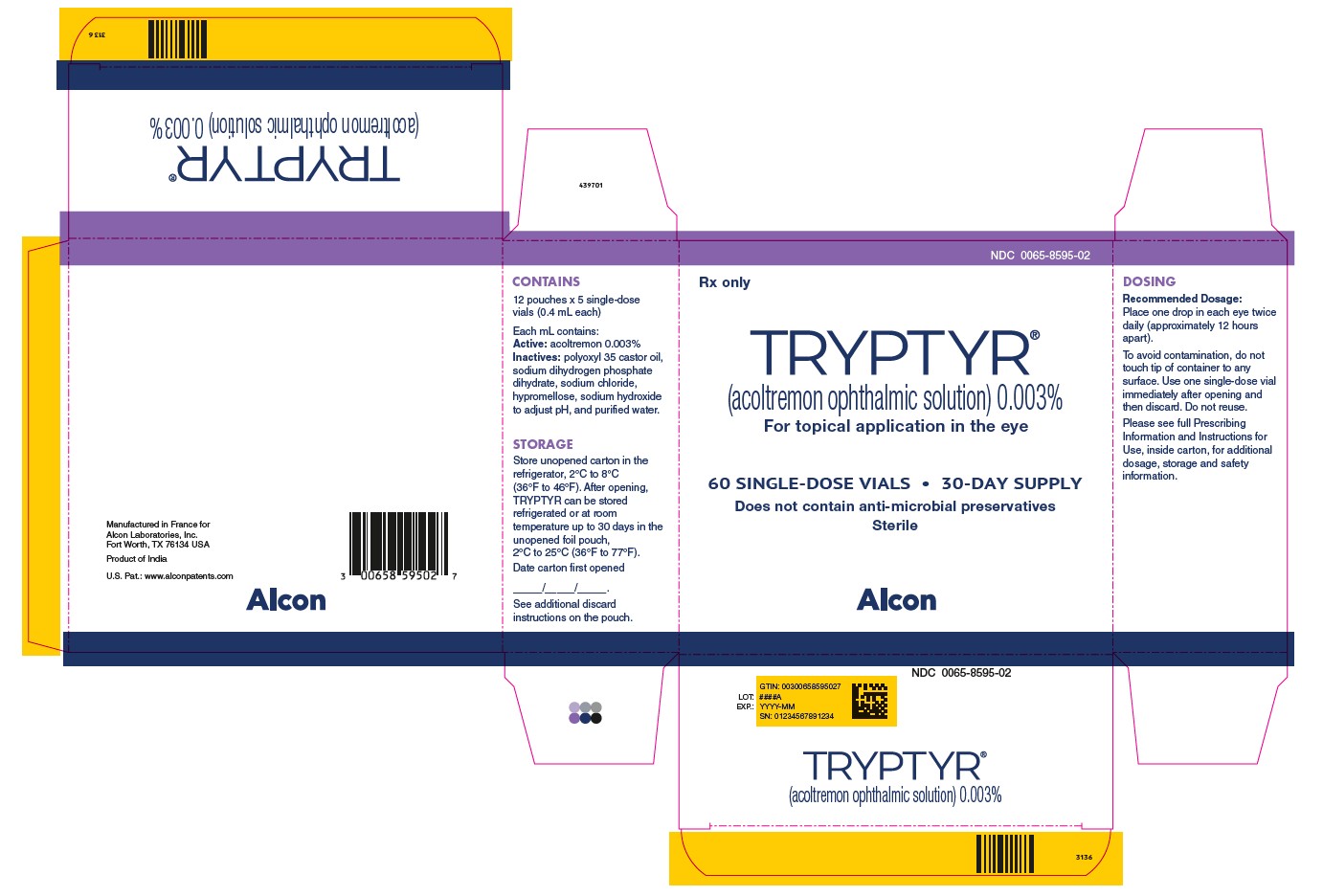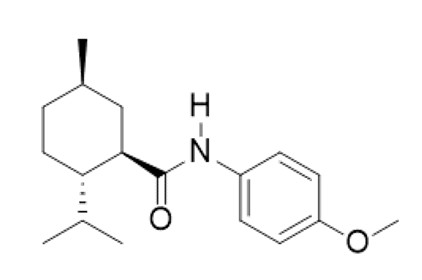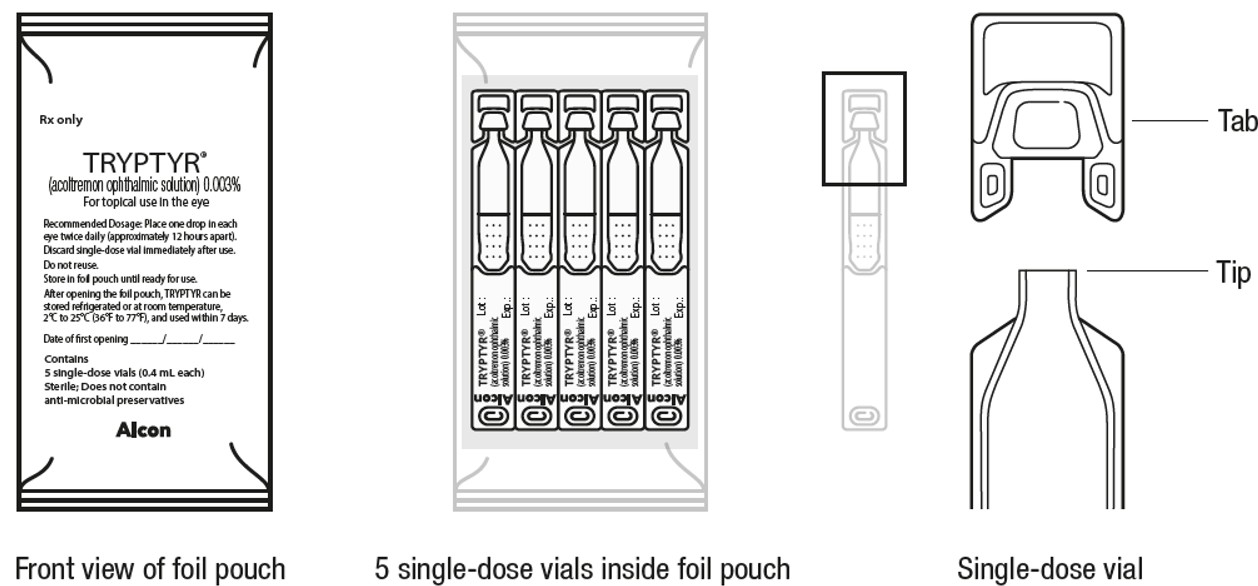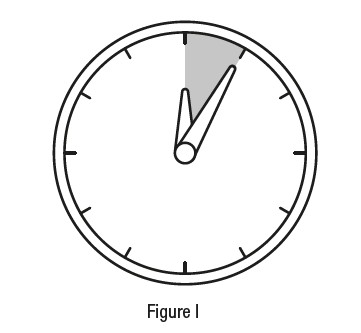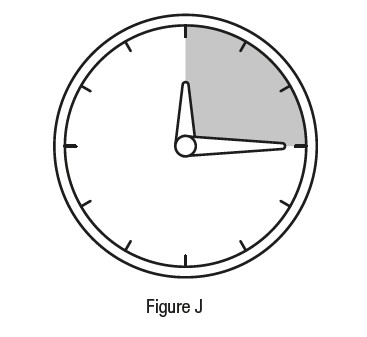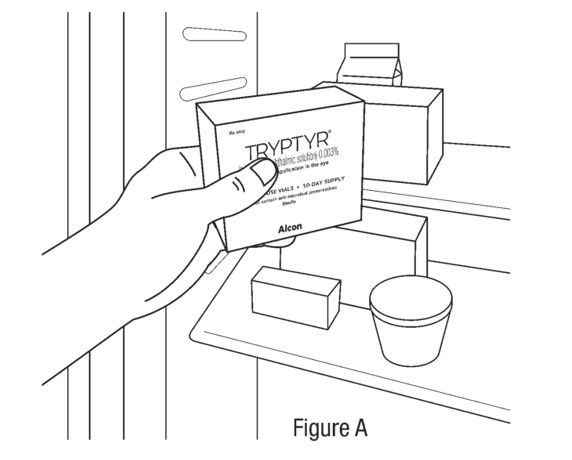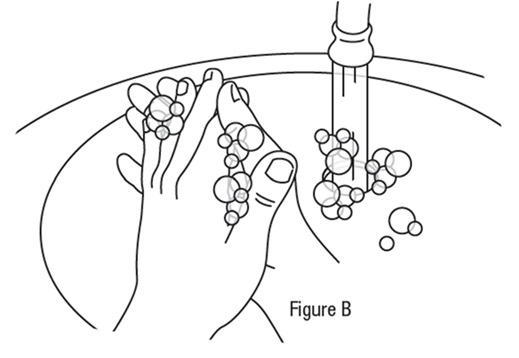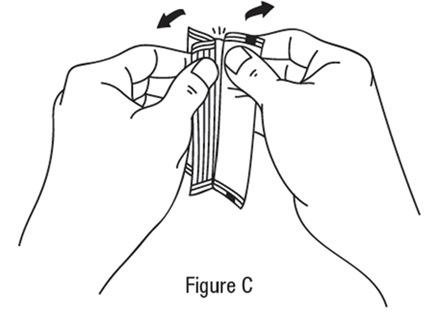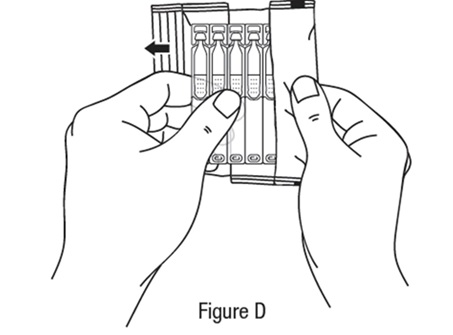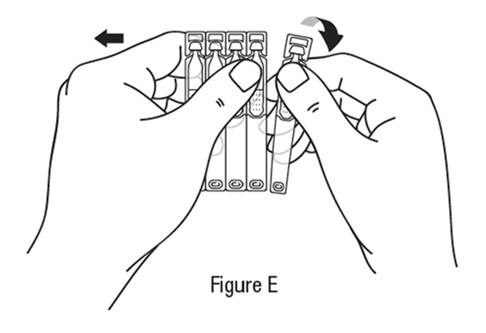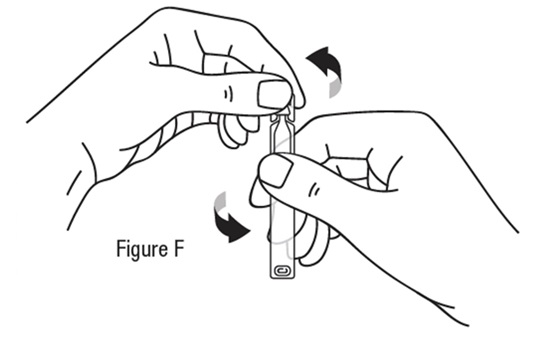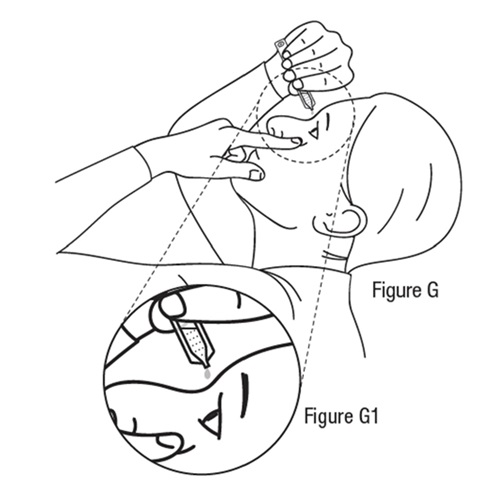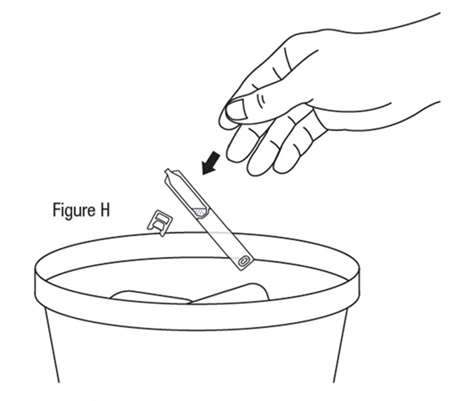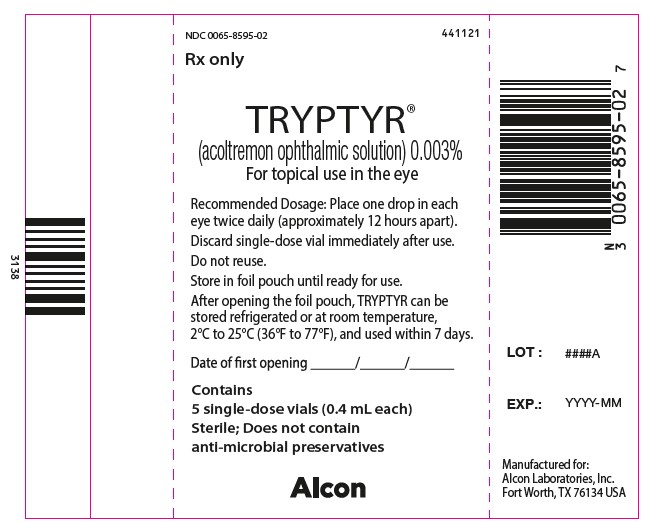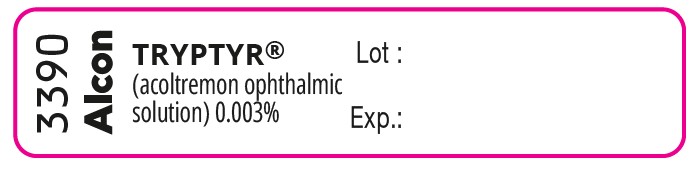 DRUG LABEL: TRYPTYR
NDC: 0065-8595 | Form: SOLUTION
Manufacturer: Alcon Laboratories, Inc.
Category: prescription | Type: HUMAN PRESCRIPTION DRUG LABEL
Date: 20251218

ACTIVE INGREDIENTS: Acoltremon .03 mg/1 mL
INACTIVE INGREDIENTS: Polyoxyl 35 Castor Oil; Sodium Phosphate, Monobasic, Dihydrate; Sodium Chloride; Hypromellose 2906 (4000 Mpa.S); Sodium Hydroxide; Water

HIGHLIGHTS OF PRESCRIBING INFORMATION

These highlights do not include all the information needed to use TRYPTYR® safely and effectively. See full prescribing information for TRYPTYR.
TRYPTYR (acoltremon ophthalmic solution) 0.003%, for topical ophthalmic use
Initial U.S. Approval: 2025

1 INDICATIONS AND USAGE

TRYPTYR is a TRPM8 thermoreceptor agonist indicated for the treatment of the signs and symptoms of dry eye disease. (1)

2 DOSAGE AND ADMINISTRATION

Instill one drop in each eye twice daily (approximately 12 hours apart). (2)

3 DOSAGE FORMS AND STRENGTHS

Ophthalmic solution: 0.003% acoltremon in a single-dose vial. (3)

4 CONTRAINDICATIONS

None. (4)

5 WARNINGS AND PRECAUTIONS

To avoid the potential for eye injury and contamination, do not touch the vial tip to the eye or other surfaces. (5.1)

6 ADVERSE REACTIONS

The most common adverse reaction was instillation site pain (50%). (6.1)

To report SUSPECTED ADVERSE REACTIONS, contact Alcon Laboratories, Inc. at 1-800-757-9780, or FDA at 1-800-FDA-1088 or www.fda.gov/medwatch.

FULL PRESCRIBING INFORMATION

1 INDICATIONS AND USAGE

TRYPTYR is indicated for the treatment of the signs and symptoms of dry eye disease.

2 DOSAGE AND ADMINISTRATION

2.1 Recommended Dosage

Instill one drop in each eye twice daily (approximately 12 hours apart).

2.2 Administration Instructions

Wash hands before use.
The single-dose vials are to be used immediately after opening and can be used to dose both eyes. Discard the single-dose vial, including any remaining contents, immediately after use.
TRYPTYR can be used concomitantly with other topical ophthalmic eye drops. If more than one topical ophthalmic drug is being used, the drugs should be administered at least five (5) minutes apart.
Contact lenses should be removed prior to the administration of TRYPTYR and may be reinserted 15 minutes following administration.
If one dose is missed, treatment should continue with the next dose.

3 DOSAGE FORMS AND STRENGTHS

TRYPTYR is a clear to slightly opalescent, colorless ophthalmic solution containing 0.003% acoltremon in a single-dose vial.

4 CONTRAINDICATIONS

None.

5 WARNINGS AND PRECAUTIONS

5.1 Potential for Eye Injury and Contamination

To avoid the potential for eye injury and contamination, do not touch the vial tip to the eye or other surfaces.

5.2 Use with Contact Lenses

TRYPTYR should not be administered while wearing contact lenses. If contact lenses are worn, they should be removed prior to administration of the solution. Lenses may be reinserted 15 minutes following administration of TRYPTYR.

6 ADVERSE REACTIONS

6.1 Clinical Trials Experience

Because clinical trials are conducted under widely varying conditions, adverse reaction rates observed in the clinical trials of a drug cannot be directly compared to rates in the clinical trials of another drug and may not reflect the rates observed in practice.

In patients with dry eye disease, 766 patients received at least one dose of TRYPTYR in four randomized controlled clinical trials across 71 sites in the United States. The most common ocular adverse reaction observed in controlled clinical studies with TRYPTYR was instillation site pain (50%). Less than 1% of patients discontinued therapy due to burning or stinging sensation in the eyes.

8 USE IN SPECIFIC POPULATIONS

8.1 Pregnancy

Risk Summary
There are no adequate and well-controlled studies on TRYPTYR in pregnant women. Systemic exposure to acoltremon from ocular administration is negligible [see Clinical Pharmacology (12.3)]. Intravenous administration of acoltremon to pregnant rats and rabbits during organogenesis did not produce embryofetal toxicity at 806- and 2151-fold the maximum recommended human ocular dose (MRHOD) of acoltremon on a mg/m^2 basis (see Data).

All pregnancies have a risk of birth defect, loss, or other adverse outcomes. In the US general population, the estimated background risk of major birth defects is 2 to 4%, and of miscarriage is 15 to 20%, of clinically recognized pregnancies.

Data

Animal Data

In embryofetal developmental studies in pregnant rats and rabbits dosed by intravenous injection daily during organogenesis from gestation days 6-17 and gestation days 7-19, respectively, no maternal or fetal toxicity was observed at 806- and 2151-fold the MRHOD of acoltremon on a mg/m^2 basis.

8.2 Lactation

Risk Summary
There are no data on the presence of acoltremon in human milk, the effects on the breastfed infant, or the effects on milk production. However, systemic exposure to acoltremon following topical ocular administration is low. The lack of clinical data during lactation precludes a clear determination of the risk of TRYPTYR to an infant during lactation; however, the developmental and health benefits of breastfeeding should be considered along with the mother’s clinical need for TRYPTYR.

8.4 Pediatric Use

The safety and effectiveness of TRYPTYR have not been established in pediatric patients.

8.5 Geriatric Use

No clinically relevant differences in safety have been observed between elderly and younger patients.

11 DESCRIPTION

TRYPTYR (acoltremon ophthalmic solution) 0.003% contains an agonist of TRPM8 ion channels. Acoltremon’s chemical name is (1R,2S,5R)-2-isopropyl-N-(4-methoxyphenyl)-5-methylcyclohexane-1-carboxamide. The molecular formula of acoltremon is C18H27NO2 and has a molecular weight of 289.42 g/mol.

Acoltremon is a white to pale yellow crystalline solid, that is insoluble in water.

TRYPTYR is a sterile, clear to slightly opalescent, colorless, isotonic aqueous solution for topical ophthalmic use, with a pH of approximately 7 and an osmolality of 280 to 330 mOsm/kg. Each mL of TRYPTYR contains active: acoltremon 0.003%; and inactives: polyoxyl 35 castor oil, sodium dihydrogen phosphate dihydrate, sodium chloride, hypromellose and purified water. Additionally, sodium hydroxide is used to adjust pH. TRYPTYR does not contain an anti-microbial preservative.

12 CLINICAL PHARMACOLOGY

12.1 Mechanism of Action

Studies in animals suggest that acoltremon, the active substance in TRYPTYR, is an agonist of transient receptor potential melastatin 8 (TRPM8) thermoreceptors. TRPM8 thermoreceptor stimulation has been shown to activate trigeminal nerve signaling leading to increased basal tear production. The exact mechanism of action for TRYPTYR in dry eye disease is unknown.

12.3 Pharmacokinetics

PK was assessed in 25 patients with dry eye disease receiving TRYPTYR administration (1 drop twice daily) on Days 1, 14, and 90. A total of three (3) (12.0%) had plasma concentrations above 20 pg/mL (the lower limit of quantification), with the highest plasma concentration of 213 pg/mL.

13 NONCLINICAL TOXICOLOGY

13.1 Carcinogenesis, Mutagenesis, Impairment of Fertility

Carcinogenicity
Long term studies in animals have not been performed to evaluate the carcinogenic potential of acoltremon.
Mutagenicity
Acoltremon was not mutagenic or clastogenic in the standard battery of genotoxicity tests including a bacterial reverse mutation assay, an in vitro chromosomal aberration assay in human peripheral lymphocytes and micronucleus assay in rats.
Impairment of Fertility
Studies to evaluate the potential effects of acoltremon on male or female fertility in animals have not been performed.

14 CLINICAL STUDIES

The efficacy of TRYPTYR for the treatment of dry eye disease was supported by two randomized, multi-center, double-masked, vehicle-controlled studies (COMET-2 [NCT-05285644] and COMET-3 [NCT-05360966]) enrolling a total of 931 dry eye patients (462 of which received TRYPTYR).

Patients were randomized to TRYPTYR or vehicle (placebo) in a 1:1 ratio and dosed twice a day for 90 days. Use of artificial tears was not allowed during the studies. The mean age was 61 years (range, 30-93 years). The majority of patients were female (74.8%). Enrollment criteria included signs (i.e., corneal fluorescein staining score [2-15] and anesthetized Schirmer tear test [2-9 mm]) and symptoms (i.e., SANDE Score [≥ 50] and Ocular Discomfort Score [≥ 50]) of dry eye disease.

Efficacy
Tear film production was measured by unanesthetized Schirmer tear test assessed using a Schirmer strip (0 - 35 mm). The average baseline unanesthetized Schirmer scores for TRYPTYR and Vehicle treated patients was 6.2 mm and 5.9 mm in the COMET-2 study, and 6.8 mm and 6.4 mm in the COMET-3 study, respectively. Of the patients treated at Day 14 (primary endpoint) with TRYPTYR, 42.6% achieved ≥ 10 mm increase in Schirmer score from baseline in the COMET-2 study and 53.2% achieved ≥ 10 mm increase in Schirmer score from baseline at Day 14 in the COMET-3 study, compared to 8.2% and 14.4% of vehicle-treated patients in the COMET-2 study and the COMET-3 study, respectively. A statistically significant improvement in tear production favoring TRYPTYR (p<0.01) was observed in both studies (Table 1).

Table 1: Percent of Patients Achieving ≥ 10 mm Improvement from Baseline in Schirmer Score at Day 14 in Patients with Dry Eye Disease
Tear Production
 | COMET-2 |  | COMET-3
 | TRYPTYR N = 230 | Vehicle N = 235 | TRYPTYR N = 232 | Vehicle N = 234
≥ 10 mm increase in tear production at Day 14 | 42.6% | 8.2% | 53.2% | 14.4%
Difference (95% CI) | 34.4% (26.9, 42.0) |  | 38.8% (30.8, 46.8)
P-value versus vehicle | < 0.01 |  | < 0.01

Consistent results were observed at all timepoints through Day 90.

16 HOW SUPPLIED/STORAGE AND HANDLING

TRYPTYR (acoltremon ophthalmic solution) 0.003% is supplied as a sterile, clear to slightly opalescent, and colorless solution in a low-density polyethylene (LDPE), single-dose vial with a 0.4 mL fill. One strip of 5 single-dose vials is packaged in a foil pouch with twelve (12) pouches in a carton.
NDC 0065-8595-02; Carton of 60 Single-Dose Vials.

Storage
Store refrigerated at 2°C to 8°C (36°F to 46°F). After opening the carton, TRYPTYR may be stored refrigerated or at room temperature at 2°C to 25°C (36°F to 77°F). If stored at room temperature, TRYPTYR should be used within 30 days, not to exceed the expiration date printed on the carton and foil pouch.

After opening each foil pouch, the single-dose vials should be used within 7 days, not to exceed the expiration date printed on the vial. Store unopened single-dose vials in the original foil pouch until ready to use.

17 PATIENT COUNSELING INFORMATION

Advise patients to read the FDA-approved patient labeling (Instructions for Use).
Potential for Eye Injury and Contamination
Advise patients not to touch the tip of the single-dose vial to their eye or to any surface in order to avoid eye injury or contamination of the solution [see Warnings and Precautions (5.1)].
Advise patients that one single-dose vial can be used to dose both eyes immediately after opening. Discard the single-dose vial, including any remaining contents, after use [see Dosage and Administration (2)].
Use With Contact Lenses
Advise patients that contact lenses should be removed prior to administration of TRYPTYR and can be reinserted 15 minutes after administration [see Warnings and Precautions (5.2)].
Use with Other Ophthalmic Drugs
Advise patients that if more than one topical ophthalmic drug is being used, the drugs should be administered at least five (5) minutes apart [see Dosage and Administration (2)].
Storage Information
Instruct patients to store unopened single-dose vials in the original foil pouch until ready to use [see How Supplied/Storage and Handling (16)].

Manufactured for Alcon Laboratories, Inc.
Fort Worth, TX 76134, USA.
U.S. Pat.: www.alconpatents.com
©2025 Alcon Inc.

INSTRUCTIONS FOR USE SECTION

INSTRUCTIONS FOR USE
TRYPTYR® [trip’tir]
(acoltremon ophthalmic solution) 0.003%
for topical ophthalmic use

This Instructions for Use contains information on how to use TRYPTYR. Read this Instructions for Use before you start using TRYPTYR and each time you get a refill. There may be new information. This leaflet does not take the place of talking to your healthcare provider about your medical condition or your treatment.

Important Information You Need to Know Before Using TRYPTYR:

- Use TRYPTYR exactly as your healthcare provider tells you to.
- TRYPTYR is for use in the eye. Each single-dose vial of TRYPTYR will give you enough medicine to treat both of your eyes. There is extra TRYPTYR in each single-dose vial in case you miss getting a drop into your eye.
- Keep the unopened single-dose vials in the original foil package until ready to use.
- Wash your hands before each use to make sure you do not infect your eyes.
- If you use TRYPTYR with other eye medicines, wait at least 5 minutes between using TRYPTYR and the other medicines.
- If you wear contact lenses, remove them before using TRYPTYR. Wait 15 minutes after dosing before putting contact lenses back in your eyes.
- If 1 dose is missed, treatment should continue at the next scheduled time.
- Use 1 drop of TRYPTYR in each eye 2 times each day. Use 1 single-dose vial in the morning and another single-dose vial in the evening, approximately 12 hours apart.
- Do not let the tip of the single-dose vial touch your eye or any other surface to avoid eye injury or infection.
- Do not use the single-dose vial or the medicine inside it if the tip touches your eye or another surface. Throw it away.
- TRYPTYR vial is for 1-time use only. Use right away after opening and do not reuse.
- Call your healthcare provider right away if you get an allergic reaction or other eye problems such as eye injury, eye infection, or eye pain. For additional safety information, see the Full Prescribing Information and talk with your healthcare provider.

Follow steps 1 to 15 each time you use TRYPTYR
Step 1

- Remove the unopened carton from the refrigerator (see Figure A).
- Check the expiration date printed on the carton.
- Write the date the carton is first opened in the space provided on the carton.

Step 2

- Open the carton.

Preparing a single-use vial
Step 3

- Wash your hands before each use to make sure you do not infect your eyes (see Figure B).

Step 4

- Take a foil pouch out of the TRYPTYR carton.
- Write the date the foil pouch is first opened in the space provided.
- Tear open the pouch (see Figure C).

Step 5

- Remove the strip of 5 single-dose vials from the foil pouch (see Figure D).

Step 6

- Pull off one single-dose vial from the strip (see Figure E).
- Place remaining vials back in the carton. Store carton at room temperature or place the carton back in the refrigerator.

Step 7

- Open the TRYPTYR single-dose vial by twisting off the tab at the top while holding the vial upright (see Figure F). Do not touch the tip of the single-dose vial or allow it to touch any surface to avoid possible eye infection.

Applying a dose of TRYPTYR to your eyes
Step 8

- Tilt your head backwards.
- If you are not able to tilt your head, lie down.

Step 9

- Gently pull your lower eyelid downwards and look up.

Step 10

- Place the tip of the TRYPTYR single-dose vial close to your eye.
- Do not allow the tip of the vial to touch your eye to avoid eye injury or infection.

Step 11

- Gently squeeze the single-dose vial and let 1 full drop of TRYPTYR coat your eye (see Figure G and G1 below).
- If a drop misses your eye, try again.
- After the drop is in your eye, gently close (do not squeeze) your eye for a few seconds.

Step 12

- Repeat Steps 8 through 11 for your other eye.
- There is enough TRYPTYR in 1 single-dose vial for both eyes.

After dosing and disposal instructions
Step 13

- After you have applied a drop to both eyes, throw away the opened single-dose vial with any remaining solution right away (see Figure H).
- Do not reuse vial.

Step 14

- Wait at least 5 minutes between using TRYPTYR and other eye drops (see Figure I).

Step 15

- If you use contact lenses, wait at least 15 minutes before placing them back in your eyes (see Figure J).

How should I store TRYPTYR?

- Store TRYPTYR in the unopened carton.
- After opening the carton, TRYPTYR may be kept refrigerated or at room temperature at 36°F to 77°F (2°C to 25°C).
- If stored at room temperature, use TRYPTYR within 30 days.
- Always check the expiration date on the vial before use. Do not store after the expiration date.
- Throw away (dispose of) unused single-dose vials 7 days after opening the foil pouch.
- Throw away (dispose of) unused TRYPTYR after 30 days if stored at room temperature.
- Throw away (dispose of) TRYPTYR after the expiration date on the carton and pouch.
- Do not leave TRYPTYR in a car, outdoors, in the sunlight, or in any other place where temperatures can go above room temperature [greater than 77°F (25°C)].
- Keep TRYPTYR and all medicines out of reach of children.

Manufactured for: Alcon Laboratories, Inc. Fort Worth, TX 76134, U.S.A.

This Instructions for Use has been approved by the U.S. Food and Drug Administration. 5/2025

PACKAGE LABEL.PRINCIPAL DISPLAY PANEL

TRYPTYR®
(acoltremon ophthalmic
solution) 0.003%
3390
Alcon
Lot:
Exp.:

NDC 0065-8595-02 441121
Rx only
TRYPTYR®
(acoltremon ophthalmic solution) 0.003%
For topical use in eye
Recommended Dosage: Place one drop in each
eye twice daily (approximately 12 hours apart).
Discard single-dose vial immediately after use.
Do not reuse.
Store in foil pouch until ready for use.
After opening the foil pouch, TRYPTYR can be
stored refrigerated or at room temperature,
2°C to 25°C (36°F to 77°F), and used within 7 days.
Date of first opening _____/_____/_____
Contains
5 single-use vials (0.4 mL each)
Sterile; Does not contain
anti-microbial preservatives
Alcon
LOT: ####A
EXP.: YYYY-MM
Manufactured for:
Alcon Laboratories, Inc.
Fort Worth, TX 76134 USA

NDC 0065-8595-02
Rx only
TRYPTYR®
(acoltremon ophthalmic solution) 0.003%
For topical application in the eye
60 SINGLE-DOSE VIALS ● 30-Day SUPPLY
Does not contain anti-microbial preservatives
Sterile
Alcon
CONTAINS
12 pouches x 5 single-dose
vials (0.4 mL each)
Each mL contains:
Active: acoltremon 0.003%
Inactives: polyoxyl 35 castor oil,
sodium dihydrogen phosphate
dihydrate, sodium chloride,
hypromellose, sodium hydroxide
to adjust pH, and purified water.
STORAGE
Store unopened carton in the
refrigerator, 2°C to 8°C
(36°F to 46°F). After opening,
TRYPTYR can be stored
refrigerated or at room
temperature up to 30 days in the
unopened foil pouch,
2°C to 25°C (36°F to 77°F).
Date carton first opened
___/___/___
See additional discard
instructions on the pouch.
DOSING
Recommended Dosage:
Place one drop in each eye twice
daily (approximately 12 hours
apart).
To avoid contamination, do not
touch tip of container to any
surface. Use one single-dose vial
immediately after opening and
then discard. Do not reuse.
Please see full Prescribing
Information and Instructions for
Use, inside carton, for additional
dosage, storage and safety
information.
Manufactured in France for
Alcon Laboratories, Inc.
Fort Worth, TX 76134 USA
Product of India
U.S. Pat.: www.alconpatents.com
NDC 0065-8595-02
GTIN: 00300658595027
LOT: ####A
EXP.: YYYY-MM
SN: 01234567891234
TRYPTYR®
(acoltremon ophthalmic solution) 0.003%
439701